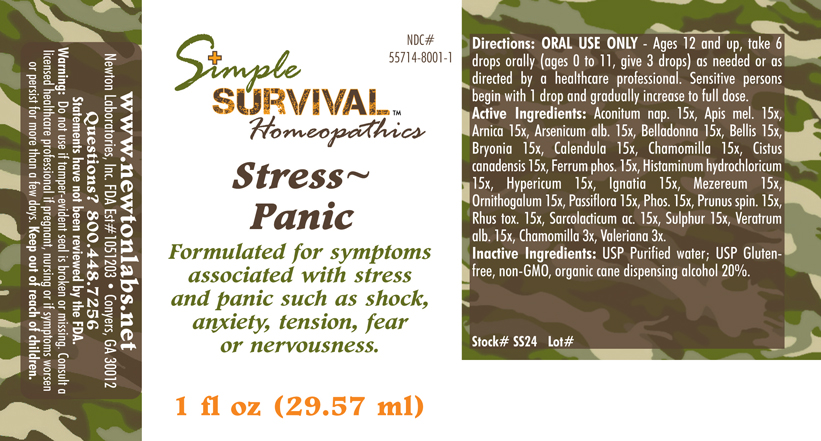 DRUG LABEL: Stress - Panic 
NDC: 55714-8001 | Form: LIQUID
Manufacturer: Newton Laboratories, Inc.
Category: homeopathic | Type: HUMAN OTC DRUG LABEL
Date: 20140415

ACTIVE INGREDIENTS: Aconitum Napellus 15 [hp_X]/1 mL; Apis Mellifera 15 [hp_X]/1 mL; Arnica Montana 15 [hp_X]/1 mL; Arsenic Trioxide 15 [hp_X]/1 mL; Atropa Belladonna 15 [hp_X]/1 mL; Bellis Perennis 15 [hp_X]/1 mL; Bryonia Alba Root 15 [hp_X]/1 mL; Calendula Officinalis Flowering Top 15 [hp_X]/1 mL; Matricaria Recutita 15 [hp_X]/1 mL; Helianthemum Canadense 15 [hp_X]/1 mL; Ferrosoferric Phosphate 15 [hp_X]/1 mL; Histamine Dihydrochloride 15 [hp_X]/1 mL; Hypericum Perforatum 15 [hp_X]/1 mL; Strychnos Ignatii Seed 15 [hp_X]/1 mL; Daphne Mezereum Bark 15 [hp_X]/1 mL; Ornithogalum Umbellatum 15 [hp_X]/1 mL; Passiflora Incarnata Flowering Top 15 [hp_X]/1 mL; Phosphorus 15 [hp_X]/1 mL; Prunus Spinosa Flower Bud 15 [hp_X]/1 mL; Toxicodendron Pubescens Leaf 15 [hp_X]/1 mL; Lactic Acid, L- 15 [hp_X]/1 mL; Sulfur 15 [hp_X]/1 mL; Veratrum Album Root 15 [hp_X]/1 mL; Valerian 3 [hp_X]/1 mL
INACTIVE INGREDIENTS: Alcohol

Stress - Panic

INDICATIONS & USAGE SECTION

Stress - Panic Formulated for symptoms associated with stress and panic such as shock, anxiety, tension, fear or nervousness.

DOSAGE & ADMINISTRATION SECTION

Directions: ORAL USE ONLY - Ages 12 and up, take 6 drops orally (ages 0 to 11, give 3 drops) as needed or as directed by a healthcare professional. Sensitive persons begin with 1 drop and gradually increase to full dose.

OTC - ACTIVE INGREDIENT SECTION

Aconitum nap. 15x, Apis mel. 15x, Arnica 15x, Arsenicum alb. 15x, Belladonna 15x, Bellis 15x, Bryonia 15x, Calendula 15x, Chamomilla 15x, Cistus canadensis 15x, Ferrum phosphoricum 15x, Histaminum hydrochloricum 15x, Hypericum 15x, Ignatia 15x, Mezereum 15x, Ornithogalum 15x, Passiflora 15x, Phos. 15x, Prunus spin. 15x, Rhus tox. 15x, Sarcolacticum ac. 15x, Sulphur 15x, Veratrum alb. 15x, Chamomilla 3x, Valeriana 3x.

OTC - PURPOSE SECTION

Formulated for symptoms associated with stress and panic such as shock, anxiety, tension, fear or nervousness.

INACTIVE INGREDIENT SECTION

Inactive Ingredients: USP Purified Water; USP Gluten-free, non-GMO, organic cane dispensing alcohol 20%.

QUESTIONS SECTION

www.newtonlabs.net Newton Laboratories, Inc. FDA Est # 1051203 - Conyers, GA 30012
Questions? 1.800.448.7256

WARNINGS SECTION

Warning: Do not use if tamper - evident seal is broken or missing. Consult a licensed healthcare professional if pregnant, nursing or if symptoms worsen or persist for more than a few days. Keep out of reach of children.

OTC - PREGNANCY OR BREAST FEEDING SECTION

Consult a licensed healthcare professional if pregnant, nursing or if symptoms worsen or persist for more than a few days.

OTC - KEEP OUT OF REACH OF CHILDREN SECTION

Keep out of reach of children.